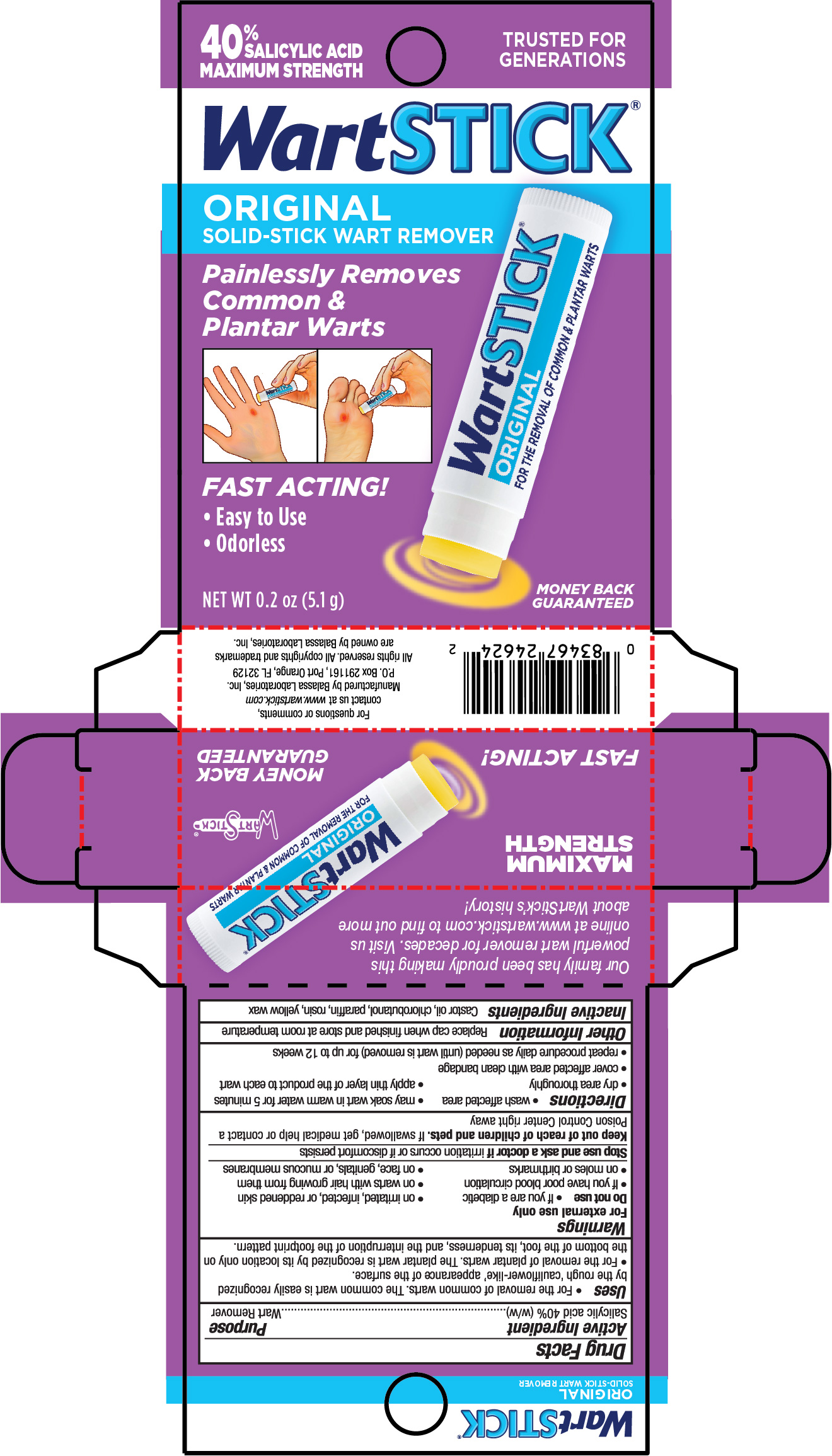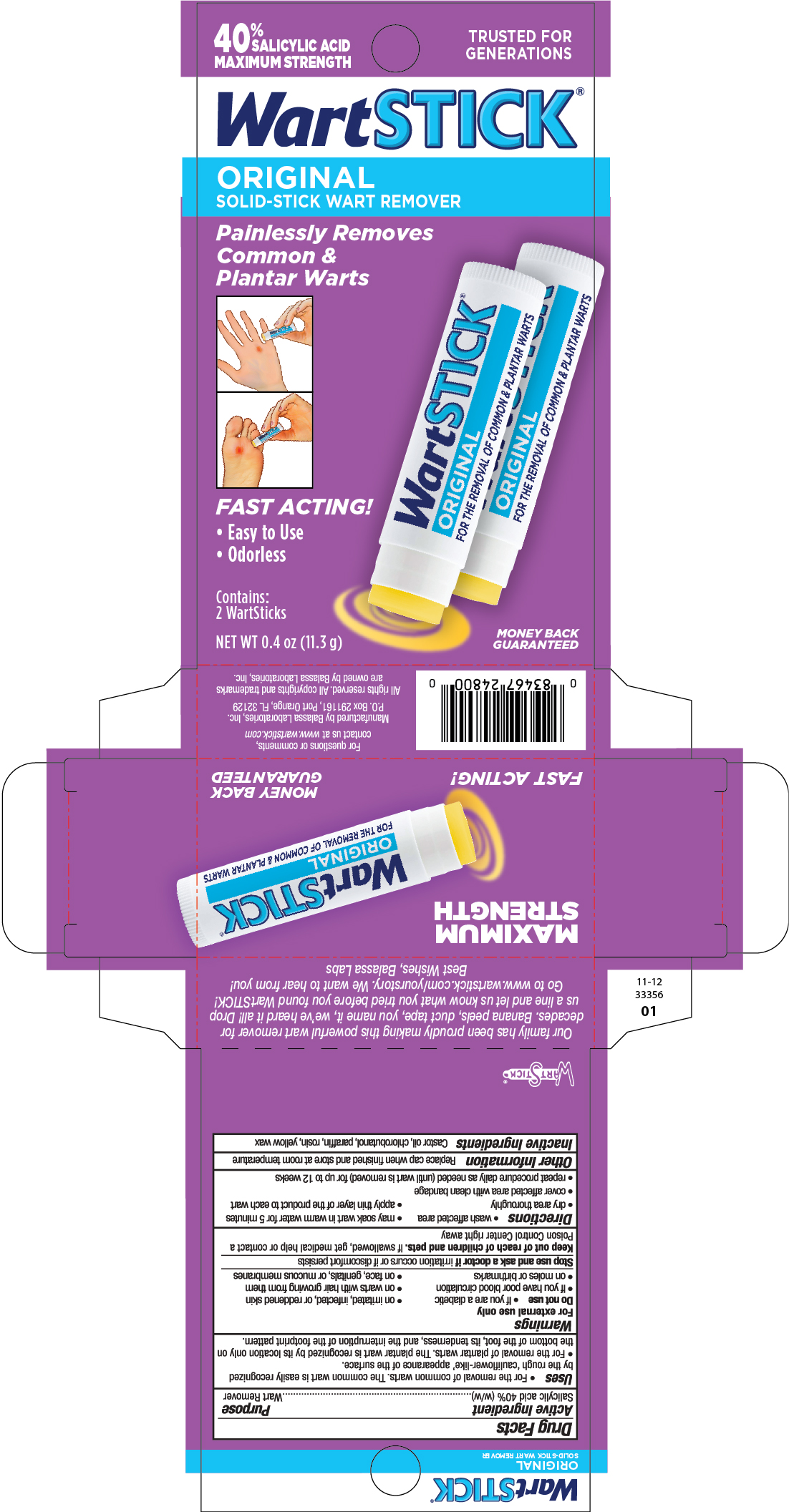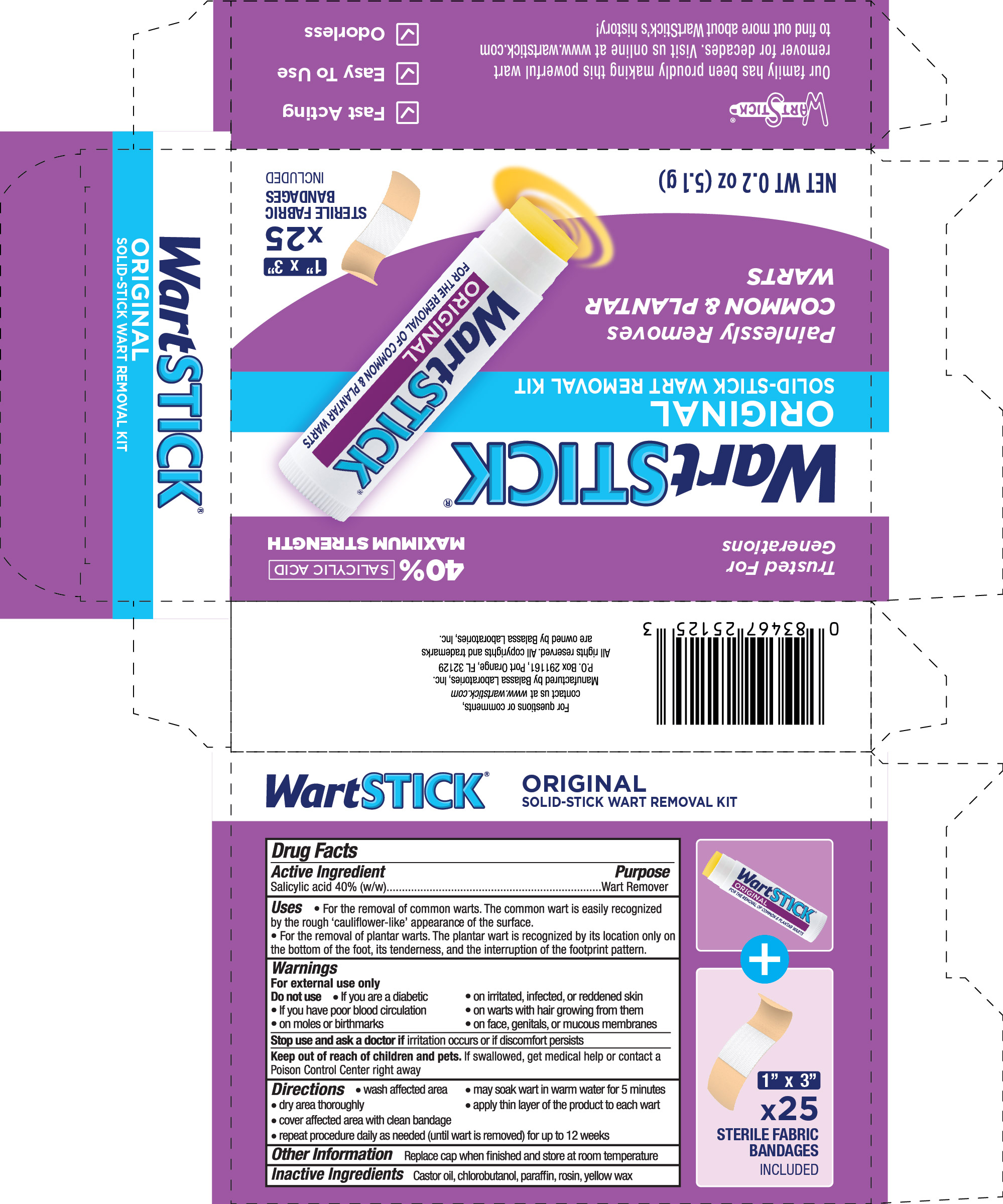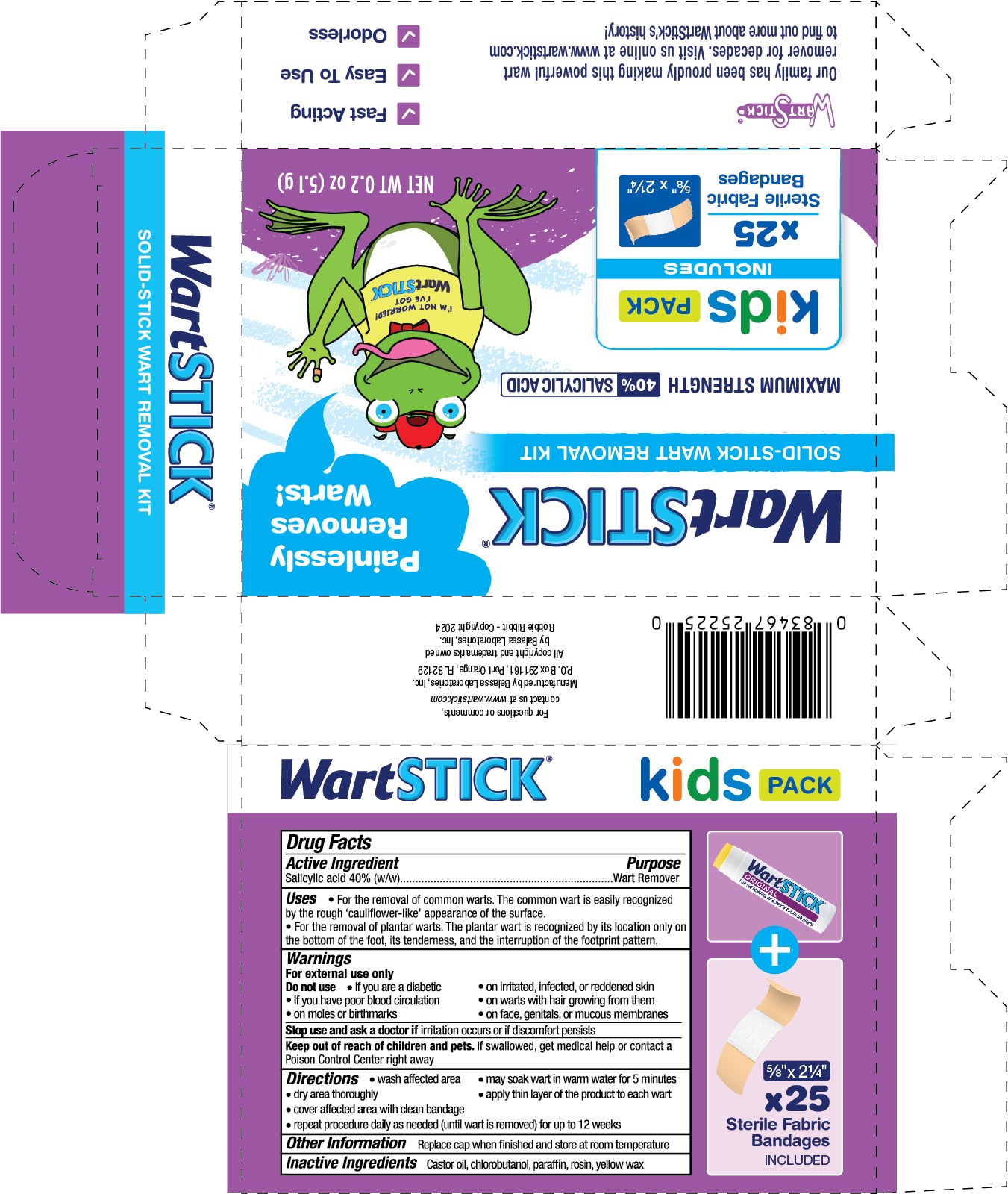 DRUG LABEL: WartStick
NDC: 10107-250 | Form: STICK
Manufacturer: Balassa Laboratories Inc.
Category: otc | Type: HUMAN OTC DRUG LABEL
Date: 20241016

ACTIVE INGREDIENTS: SALICYLIC ACID 0.4 g/1 g
INACTIVE INGREDIENTS: CHLOROBUTANOL; CASTOR OIL; YELLOW WAX; PARAFFIN; ROSIN

WartStick Wart Remover

Active Ingredient

Salicylic acid 40% (w/w)

Purpose

Wart remover

Uses

- For the removal of common warts. The common wart is easily recognized by the rough "cauliflower-like" appearance of the surface.
- For the removal of plantar warts. The plantar wart is recognized by its location only on the bottom of the foot, its tenderness, and the interruption of the footprint pattern.

Warnings

For external use only.

Do not use

- if you are a diabetic
- on irritated, infected, or reddened skin
- if you have poor blood circulation
- on warts with hair growing from them
- on moles or birthmarks
- on face, genitals, or mucous membranes

Stop use and ask a doctor if

irritation occurs or discomfort persists

Keep out of reach of children and pets.

If swallowed, get medical help or contact a Poison Control Center right away.

Directions

- Wash affected area
- May soak in warm water for 5 minutes
- Dry area thoroughly
- Keeping the product off the surrounding skin, apply a thin layer of the product to each wart
- Cover affected area with clean bandage
- Repeat procedure daily as needed (until wart is removed) for up to 12 weeks

Other Information

Replace cap when finished and store at room temperature

Inactive Ingredients

Castor oil, chlorobutanol, paraffin, rosin, yellow wax

PRINCIPAL DISPLAY PANEL - 5.1 g Tube in Carton - NDC 10107-250-02

40% SALICYLIC ACID

MAXIMUM STRENGTH

TRUSTED FOR GENERATIONS

WartSTICK ®

ORIGINAL SOLID-STICK WART REMOVER

Painlessly Removes Common & Plantar Warts

Fast Acting!

- Easy to Use
- Odorless

NET WT 0.2 OZ (5.1g)

MONEY BACK GUARANTEED

PRINCIPAL DISPLAY PANEL - Two 5.1 g Tubes in Carton - NDC 10107-250-03

40% SALICYLIC ACID

MAXIMUM STRENGTH

TRUSTED FOR GENERATIONS

WartSTICK ®

ORIGINAL Solid-Stick Wart Remover

Painlessly Removes Common & Plantar Warts

Fast Acting!

- Easy to Use
- Odorless

Contains: 2 WartSticks

NET WT 0.4 OZ (11.3g)

MONEY BACK GUARANTEED

PRINCIPAL DISPLAY PANEL - 5.1 g Tube in Carton, with 25 1"x3" bandages - NDC 10107-250-20

40% SALICYLIC ACID

MAXIMUM STRENGTH

TRUSTED FOR GENERATIONS

WartSTICK ®

ORIGINAL SOLID-STICK WART REMOVAL KIT

Painlessly Removes Common & Plantar Warts

NET WT 0.2 OZ (5.1g)

25 1" x 3" STERILE FABRIC BANDAGES INCLUDED

PRINCIPAL DISPLAY PANEL - 5.1 g Tube in Carton, with 25 0.625" x 2.25" bandages - NDC 10107-250-21

WartSTICK ®

SOLID-STICK WART REMOVAL KIT

MAXIMUM STRENGTH 40% SALICYLIC ACID

Painlessly Removes Warts!

kids PACK INCLUDES x25 Sterile Fabric Bandages (5/8" x 2 1/4")

NET WT 0.2 OZ (5.1g)